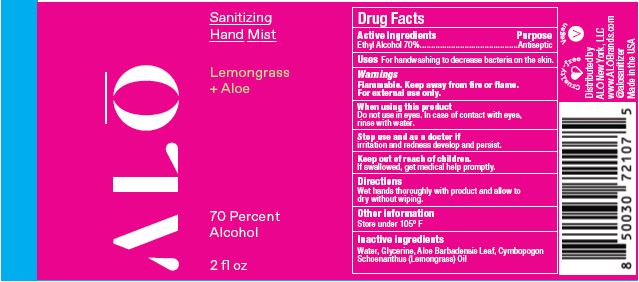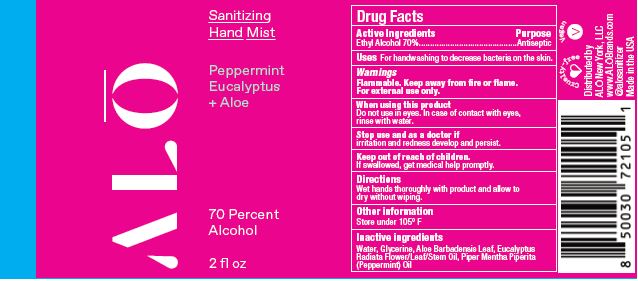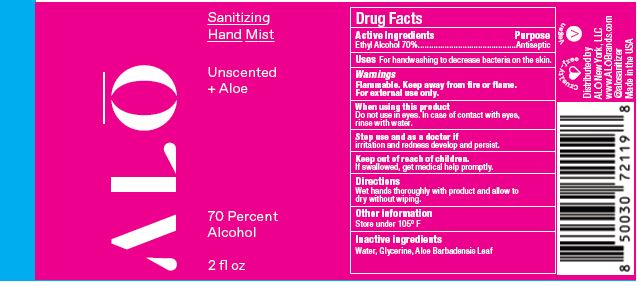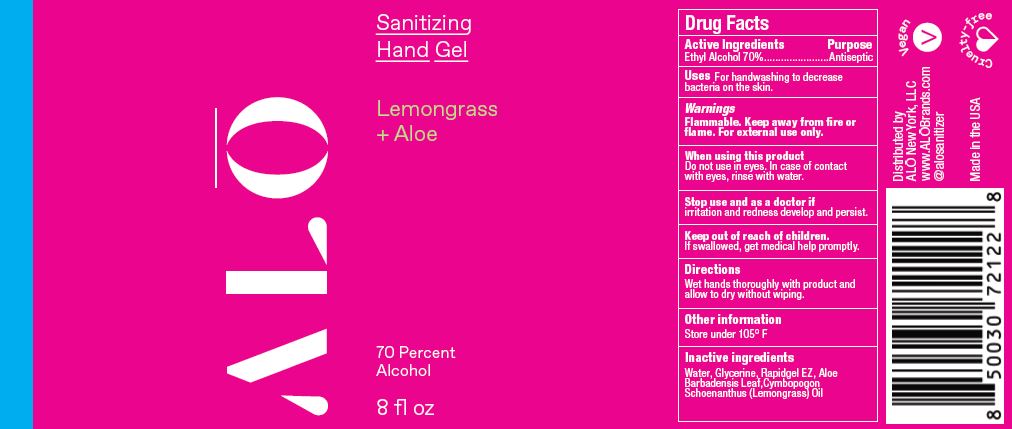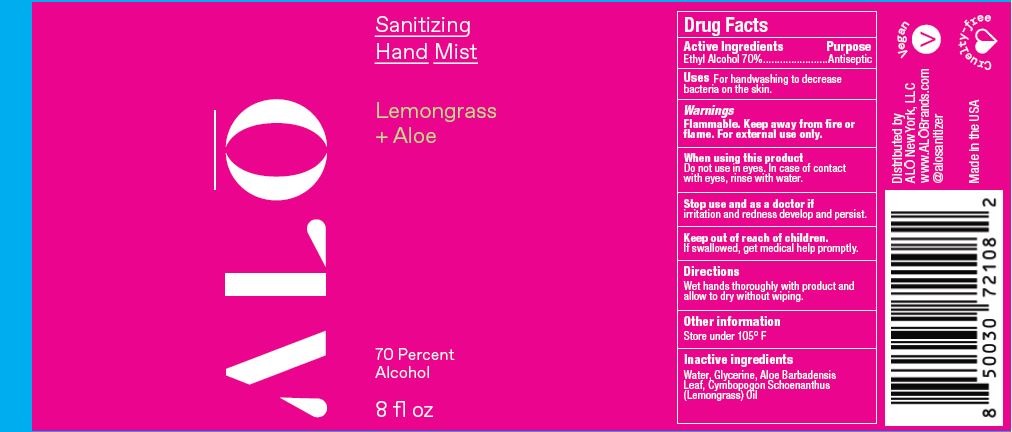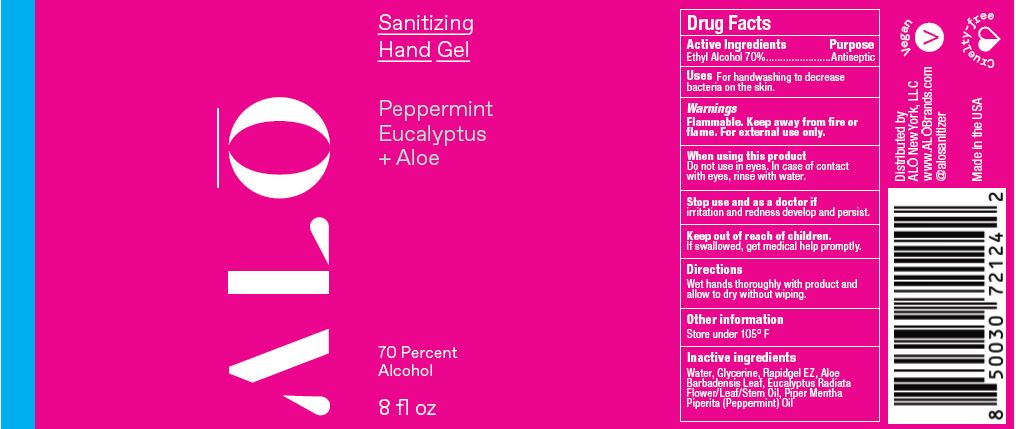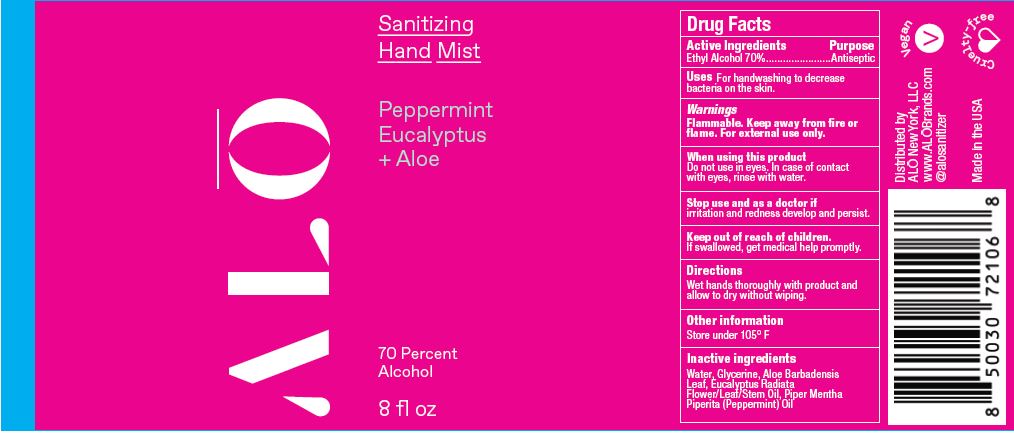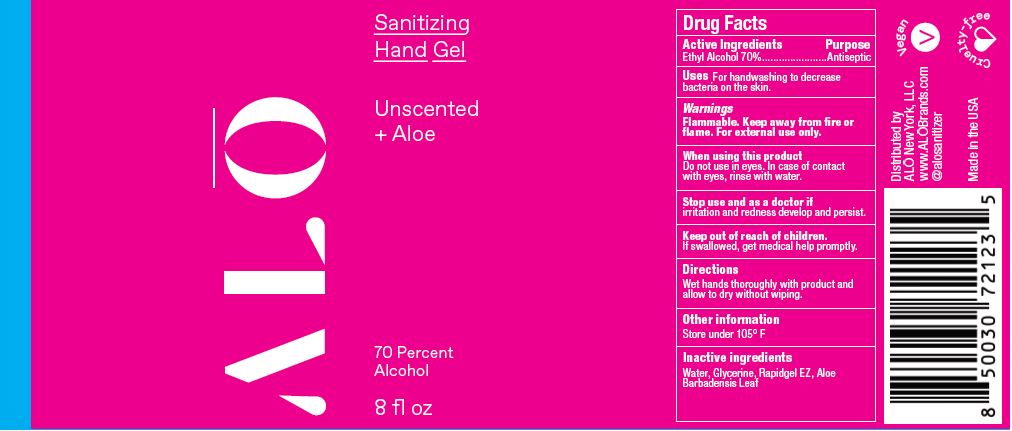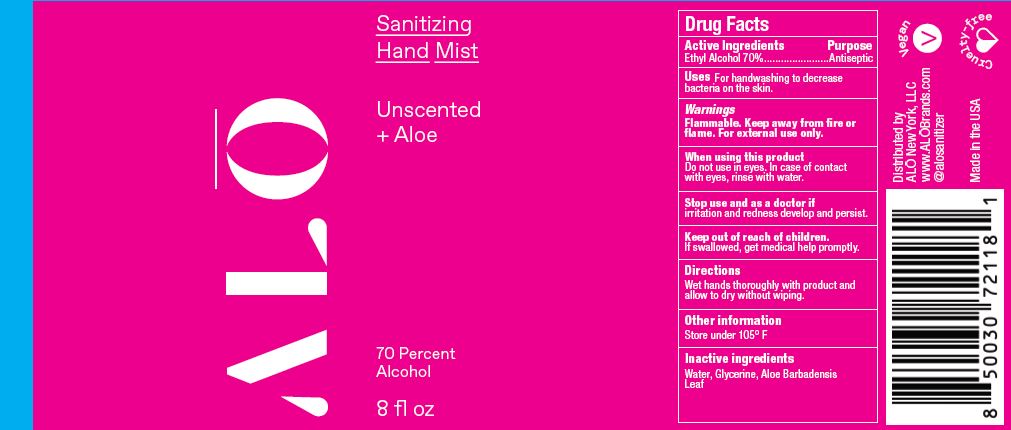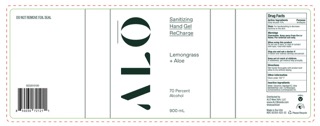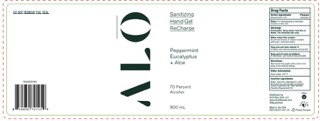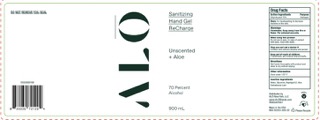 DRUG LABEL: Sanitizing Hand Mist Unscented
NDC: 82355-010 | Form: SPRAY
Manufacturer: ALO New York LLC
Category: otc | Type: HUMAN OTC DRUG LABEL
Date: 20241203

ACTIVE INGREDIENTS: ALCOHOL 70 mL/100 mL
INACTIVE INGREDIENTS: ALOE; GLYCERIN; WATER

ALO Brands Hand Sanitzer

Active ingredients

Ethyl Alcoahol

Purpose

Antiseptic

Uses

For handwashing to decrease bacteria on the skin

Warnings

Flammable. Keep away from fire or flame. For external use only.

When using this product

Do not use in eyes. In case of contact with eyes, rinse with water.

Stop use and ask doctor if

irritation and redness develop and persist.

Keep out of reach of chidren.

If swallowed, get medical help promptly.

Directions

Wet hands thoroughly with product and allow to dry without wiping.

Other information

Store under 105°F

Inactive Ingredients

NDC 80588-010:
Water, Glycerine, Aloe Barbadensis Leaf
NDC 80588-011:
Water, Glycerine, Alce Barbadensis Leaf, Eucalyptus Radiata Flower/leaf/Stem Oil, Piper Mentha Piperita (Peopermint) Oil

NDC 80588-012:

Water, Glycerine, Aloe Barbadensis Leaf, Cymbopogon Schoenanthus (Lemongrass) Oil

NDC 80588-020:
Water, Glyperine, Rapidgel EZ. Aloe barbadensis Leaf
NDC 80588-011:
Water. Glycerine, Rapidgel EZ. Aloe Barbadensis Leaf. Eucalyptus Radiate Flower/Leaf/Stem Oil, Piper Mentha Piperita (Peppermint) Oil

NDC 80588-012:
Water, Glycerine, Rapidgel EZ. Aloe Barbadensis Leaf, Cymbopogon Schoenanthus (Lemongrass) Oil